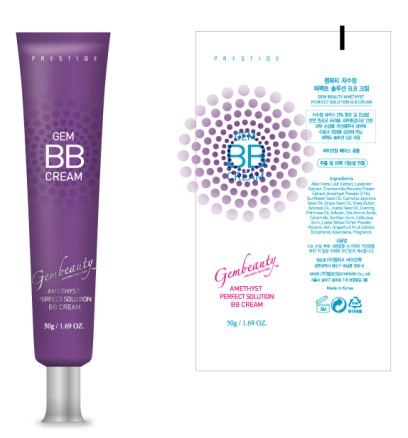 DRUG LABEL: GEM BEAUTY AMETHYST PERFECT SOLUTION BB CREAM
NDC: 50030-004 | Form: CREAM
Manufacturer: GEMPARK CO LTD
Category: otc | Type: HUMAN OTC DRUG LABEL
Date: 20091109

ACTIVE INGREDIENTS: ALOE FEROX LEAF 6.65 g/50 g

ACTIVE INGREDIENT

INGREDIENTS:

Aloe Ferox Leaf Extract, Lavender Extract, Chamomilla Recutita Flower Extract, Amethyst Powder, Sunflower Seed Oil, Camellia Japonica Seed Oil, Grape Seed Oil, Shea Butter, Avacado Oil, Jajoba Seed Oil, Evening Primrose Oil, Arbutin, Silk Amino Acids, Ceramide, Xanthan Gum, Cellulose Gum, Loess Yellow Ocher Powder, Volcanic Ash, Grapefruit Fruit Extract, Tocopherol, Adenosine, Fragrance

PACKAGE LABEL

Label2